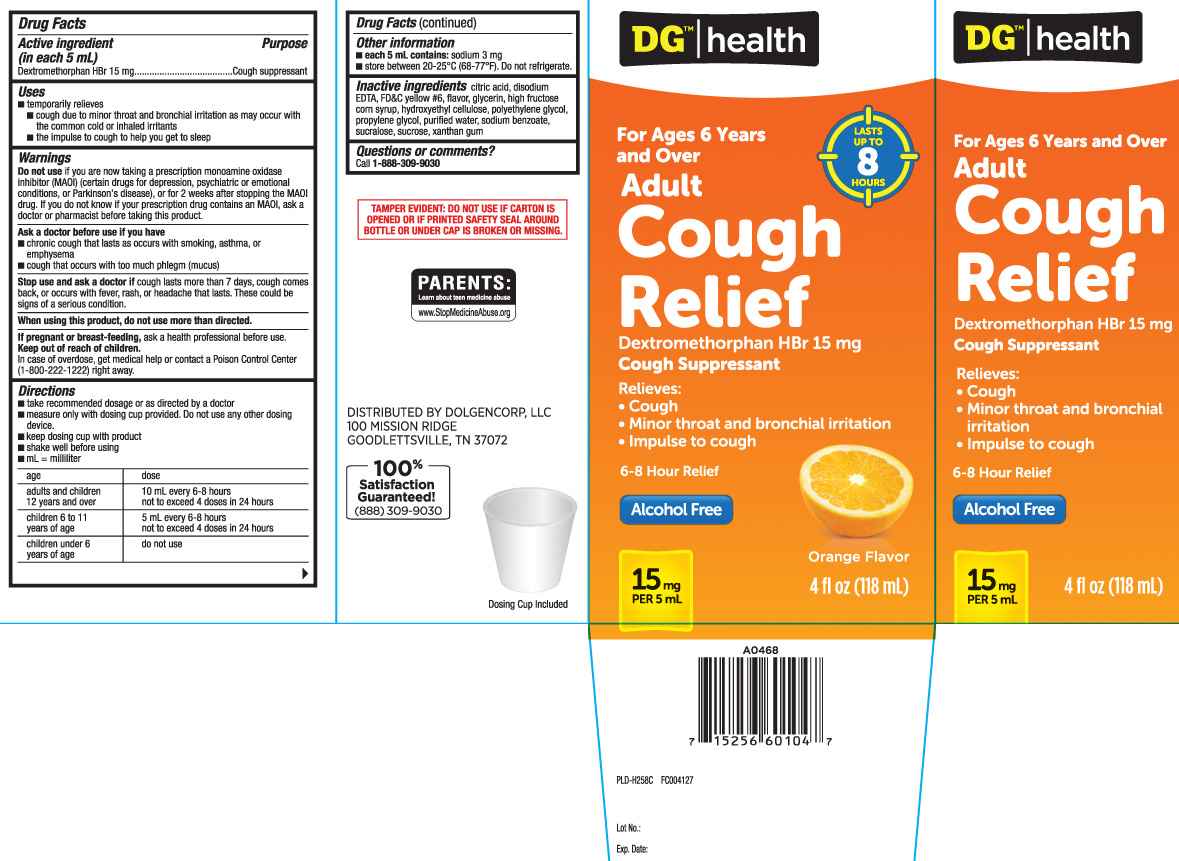 DRUG LABEL: Cough Relief
NDC: 55910-309 | Form: LIQUID
Manufacturer: Dolgencorp, Inc.  (DOLLAR GENERAL & REXALL)
Category: otc | Type: HUMAN OTC DRUG LABEL
Date: 20241014

ACTIVE INGREDIENTS: DEXTROMETHORPHAN HYDROBROMIDE 15 mg/5 mL
INACTIVE INGREDIENTS: ANHYDROUS CITRIC ACID; WATER; EDETATE DISODIUM; FD&C YELLOW NO. 6; GLYCERIN; HIGH FRUCTOSE CORN SYRUP; HYDROXYETHYL CELLULOSE (1500 MPA.S AT 1%); POLYETHYLENE GLYCOL, UNSPECIFIED; PROPYLENE GLYCOL; SODIUM BENZOATE; SUCRALOSE; SUCROSE; XANTHAN GUM

Drug Facts

Active ingredient (in each 5 mL)

Dextromethorphan HBr 15 mg

Purpose

Cough suppressant

Uses

- temporarily relieves
  - cough due to minor throat and bronchial irritation as may occur with the common cold or inhaled irritants
  - the impulse to cough to help you get to sleep

Warnings

Do not use

- if you are now taking a prescription monoamine oxidase inhibitor (MAOI) (certain drugs for depression, psychiatric or emotional conditions, or Parkinson's disease), or for 2 weeks after stopping the MAOI drug. If you do not know if your prescription drug contains an MAOI, ask a doctor or pharmacist before taking this product.

Ask a doctor before use if you have

- cough that occurs with too much phlegm (mucus)
- chronic cough that lasts as occurs with smoking, asthma, or emphysema

When using this product,

do not use more than directed

Stop use and ask a doctor if

cough lasts more than 7 days, cough comes back, or occurs by fever, rash or headache that lasts. These could be signs of a serious condition.

If pregnant or breast-feeding,

ask a health professional before use.

Keep out of reach of children.

In case of overdose, get medical help or contact a Poison Control Center (1-800-222-1222) right away.

Directions

- take recommended dosage or as directed by a doctor
- measure only with dosing cup provided. Do not use any other dosing device
- keep dosing cup with product
- shake well before using
- mL=milliliter

age | dose
adults and children 12 years and over | 10 mL every 6-8 hours not to exceed 4 doses in 24 hours,
children 6 to 11 years of age | 5 mL every 6-8 hours not to exceed 4 doses in 24 hours
children under 6 years of age | do not use

Other information

- each 5 mL contains: sodium 3 mg
- store between 20-25ºC (68-77ºF). Do not refrigerate.

Inactive ingredients

anhydrous citric acid, disodium EDTA, FD&C yellow #6, flavor, glycerin, high fructose corn syrup, hydroxyethyl cellulose, polyethylene glycol, propylene glycol, purified water, sodium benzoate, sucralose, sucrose, xanthan gum

Questilons or comments?

Call 1-888-309-9030

Principal Display Panel

For Ages 6 Years and over

Adult

Cough Relief

Dextromethorphan HBr 15 mg

Cough suppressant

Relieves:

- Cough
- Minor throat and bronchial irritation
- impulse to cough

6-8 Hour Relief

Alcohol free

FL OZ (mL)

Orange flavor

Dosing Cup Included

TAMPER EVIDENT: DO NOT USE IF CARTON IS OPENED OR IF PRINTED SAFETY SEAL AROUND BOTTLE OR UNDER CAP IS BROKEN OR MISSING.

DISTRIBUTED BY DOLGENCORP, LLC

100 MISSION RIDGE

GOODLETTSVILLE, TN 37072

Package Label

DOLLAR GENERAL Adult Cough Relief